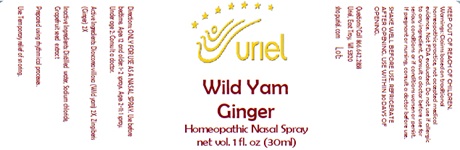 DRUG LABEL: Wild Yam Ginger
NDC: 48951-9283 | Form: SPRAY
Manufacturer: Uriel Pharmacy Inc
Category: homeopathic | Type: HUMAN OTC DRUG LABEL
Date: 20241203

ACTIVE INGREDIENTS: DIOSCOREA VILLOSA ROOT 2 [hp_X]/1 mL; GINGER 2 [hp_X]/1 mL
INACTIVE INGREDIENTS: WATER; SODIUM CHLORIDE; CITRUS PARADISI SEED

Wild Yam Ginger

INDICATIONS AND USAGE

Directions: ONLY FOR USE AS A NASAL SPRAY.

DOSAGE AND ADMINISTRATION

Use before bedtime. Ages 12 and older: 1-2 sprays. Ages 2-11: 1 spray. Under age 2: Consult a doctor.

ACTIVE INGREDIENT

Active Ingredients: Dioscorea villosa (Wild yam) 2X, Zingiberis (Ginger) 2X

INACTIVE INGREDIENT

Inactive Ingredients: Distilled water, Sodium chloride, Grapefruit seed extract

Prepared using rhythmical processes.

PURPOSE

Use: Temporary relief of snoring.

KEEP OUT OF REACH OF CHILDREN.

WARNINGS

Warnings: Claims based on traditional homeopathic practice, not accepted medical evidence. Not FDA evaluated. Do not use if allergic to any ingredient. Consult a doctor before use for serious conditions or if conditions worsen or persist. If pregnant or nursing, consult a doctor before use. Do not use if safety seals on box are broken or missing.
SHAKE WELL BEFORE USE.
REFRIGERATE AFTER OPENING.
USE WITHIN 30 DAYS OF OPENING.

Questions? Call 866.642.2858
Uriel, East Troy, WI 53120
shopuriel.com Lot: